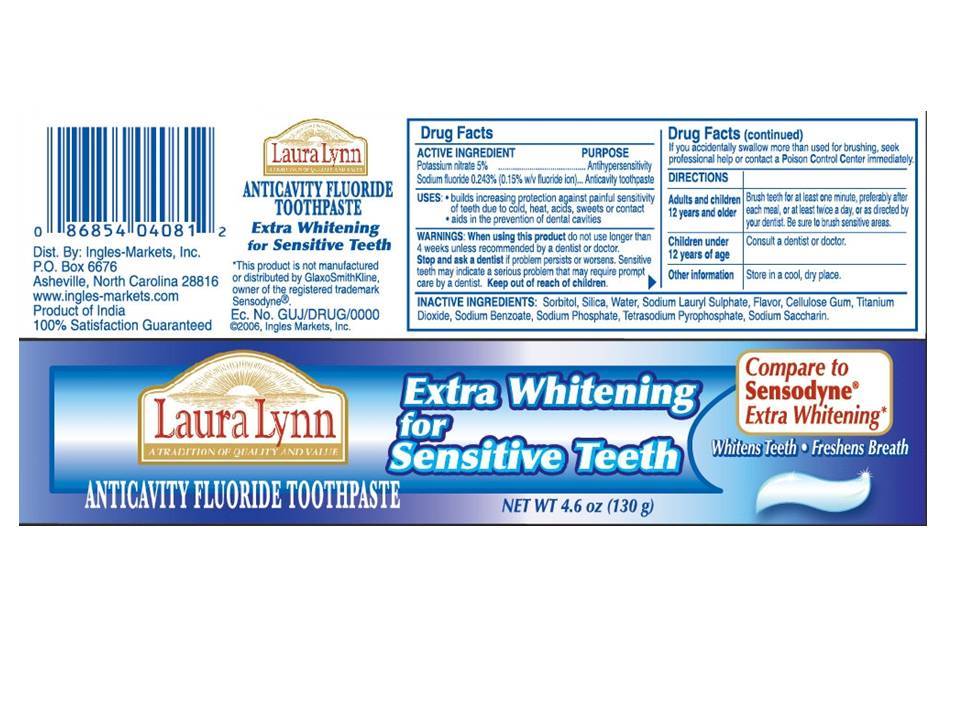 DRUG LABEL: Laura Lynn Extra Whitening Sensitive
NDC: 62936-0043 | Form: PASTE
Manufacturer: Ingles Market Inc
Category: otc | Type: HUMAN OTC DRUG LABEL
Date: 20110412

ACTIVE INGREDIENTS: POTASSIUM NITRATE 5 mg/1 g; SODIUM FLUORIDE 2.43 mg/1 g
INACTIVE INGREDIENTS: SORBITOL; SILICON DIOXIDE; Water; SODIUM LAURYL SULFATE; CROSCARMELLOSE SODIUM; TITANIUM DIOXIDE; SODIUM BENZOATE; SODIUM PHOSPHATE; SODIUM PYROPHOSPHATE; SACCHARIN SODIUM

Laura Lynn Extra Whitening for Sensitive Teeth

Active Ingredients

Potassium nitrate 5%........................................... Antihypersensitivity

Sodium Fluoride 0.243% (0.15% w/v fluoride ion).... Anticavity toothpaste

USES

- Builds increasing protection against painful sensitivity of teeth due to cold, heat, acids, sweets or contact
- Aids in the prevention of dental cavities

When using this product do not use longer than 4 weeks unless recommended by a dentist or doctor. Stop and ask a dentist if problems persists or worsens. Sensitive teeth may indicate a serious problem that may require prompt care by a dentist. Keep out of reach of children.

Directions

Adults and children 12 years and older Brush teeth for at least one minute, preferably after each meal, or at least twice a day or as directed by your dentist. Be sure to brush sensitive areas.
Children under 12 years of age Consult a dentist or doctor
Other information Store in a cool, dry place.

Inactive ingredients

Sorbitol, Silica, Water, Sodium Lauryl Sulphate, Flavor, Cellulose Gum,Titanium Dioxide, Sodium Benzoate, Sodium Phosphate, Tetrasodium Pyrophosphate, Sodium Saccharin